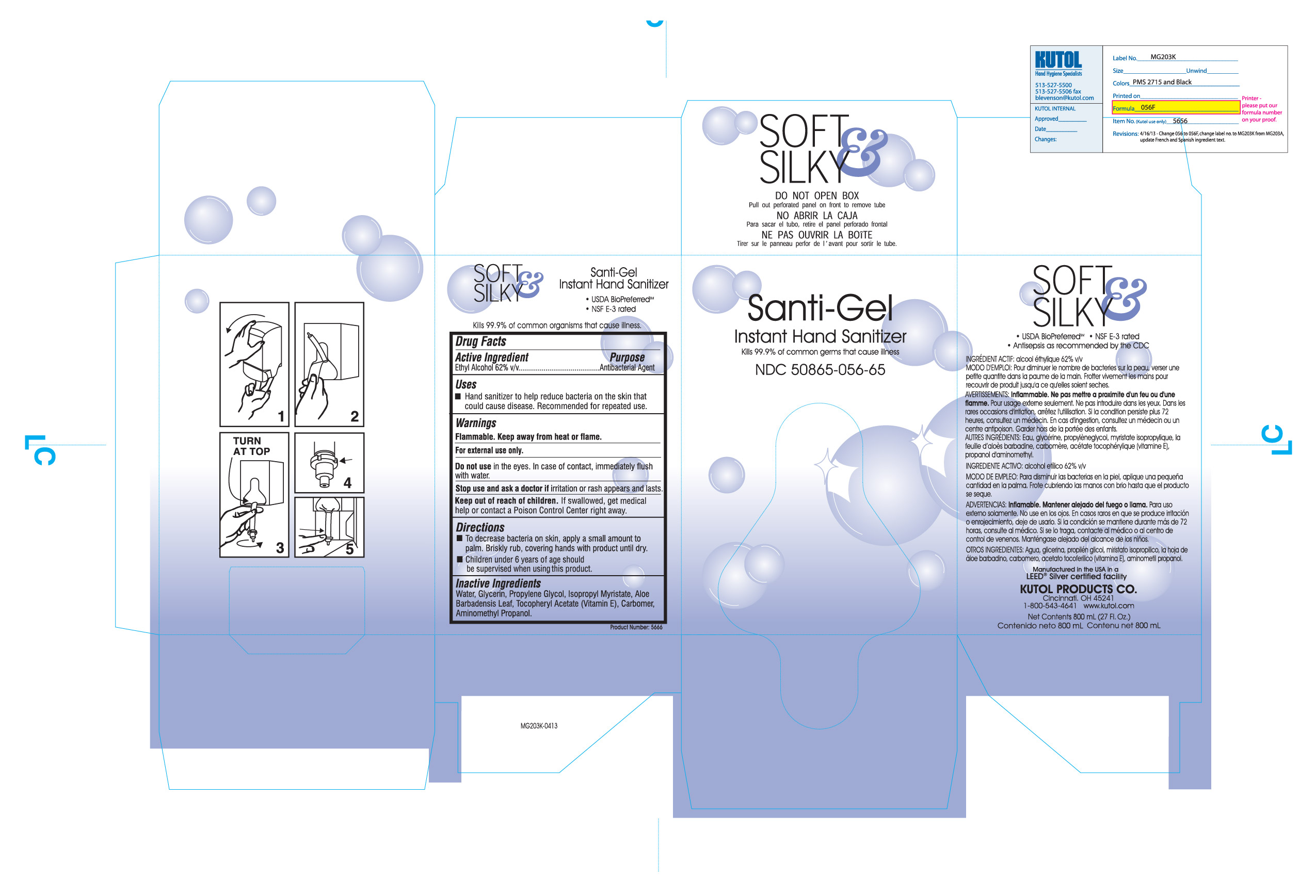 DRUG LABEL: Santi-Gel Instant Hand Sanitizer
NDC: 50865-056 | Form: SOLUTION
Manufacturer: Kutol Products Company, Inc.
Category: otc | Type: HUMAN OTC DRUG LABEL
Date: 20241218

ACTIVE INGREDIENTS: ALCOHOL 62.5 mL/100 mL
INACTIVE INGREDIENTS: POLYACRYLIC ACID (250000 MW); WATER; GLYCERIN; PROPYLENE GLYCOL; ISOPROPYL MYRISTATE; AMINOMETHYLPROPANOL; ALOE VERA LEAF; .ALPHA.-TOCOPHEROL ACETATE, DL-

Santi-Gel Instant Hand Sanitizer

WARNINGS

Flammable. Keep away from heat or flame.

For external use only.

Do not use in the eyes. In case of contact, immediately flush with water.

Stop use and ask a doctor if irritation or rash appears and lasts.

Keep out of reach of children. If swallowed, get medical help or contact a Poison Control Center right away.

ACTIVE INGREDIENT

Ethyl Alcohol 62% v/v.........Antibacterial Agent

Keep out of reach of children. If swallowed, get medical help or contact a Poison Control Center right away.

INACTIVE INGREDIENT

Water, Glycerin, Propylene Glycol, Isopropyl Mryistate, Aloe Barbadensis leaf, Tocopheryl Acetate (Vitamin E), Carbomer, Aminomethyl Propanol

DOSAGE AND ADMINISTRATION

To decrease bacteria on skin, apply a small amount to palm. Briskly rub, covering hands with product until dry.

Children under 6 years of age should be supervised when using this product.

PURPOSE

Hand Sanitizer to help reduce bacteria on the skin that could cause disease. Recommended for repeated use.

INDICATIONS AND USAGE

Hand Sanitizer to help reduce bacteria on the skin that could cause disease. Recommended for repeated use.

Do not use in the eyes. In case of contact, immediately flush with water.

Stop use and ask a doctor if irritation or rash appears and lasts.

Keep out of reach of children. If swallowed, get medical help or contact a Poison Control Center right away.

PACKAGE LABEL

50865-056-65.jpg